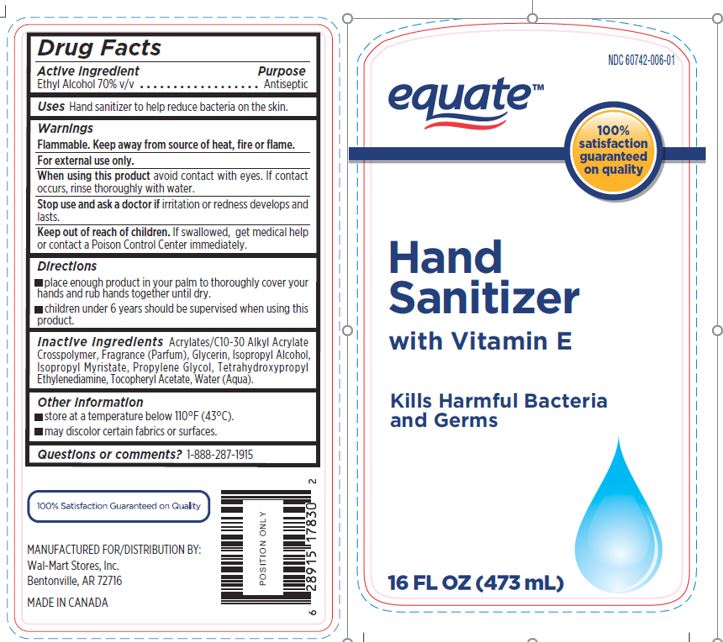 DRUG LABEL: EQUATE HAND SANITIZER
NDC: 60742-006 | Form: GEL
Manufacturer: BELVEDERE INTERNATIONAL INC.
Category: otc | Type: HUMAN OTC DRUG LABEL
Date: 20171115

ACTIVE INGREDIENTS: ALCOHOL 70 mL/100 mL
INACTIVE INGREDIENTS: WATER; ISOPROPYL ALCOHOL; GLYCERIN; ISOPROPYL MYRISTATE; ALPHA-TOCOPHEROL ACETATE; CARBOMER COPOLYMER TYPE B (ALLYL PENTAERYTHRITOL CROSSLINKED); EDETOL; PROPYLENE GLYCOL

uses

HAND SANITIZER TO HELP REDUCE BACTERIA ON THE SKIN

Directions

PLACE ENOUGH PRODUCT IN YOUR PALM TO THOROUGHLY COVER YOUR HANDS AND RUB HANDS TOGETHER UNTIL DRY

CHILDREN UNDER 6 YEARS SHOULD BE SUPERVISED WHEN USING THIS PRODUCT

Inactive ingredients

ACRYLATES/C10-30 ALKYL ACRYLATE CROSSPOLYMER, FRAGRANCE, GLYCERIN, ISOPROPYL ALCOHOL, ISOPROPYL MYRISTATE, PROPYLENE GLYCOL, TETRAHYDROXYPROPYL ETHYLENEDIAMINE, TOCOPHERYL ACETATE, WATER

Active Ingredient

ETHYL ALCOHOL 70%

Keep out of reach of children, in case of accidental ingestion, get medical help or contact a Poison Control Center immediately.

Warnings

FLAMMABLE. KEEP AWAY FROM SOURCE OF HEAT, FIRE OR FLAME.

FOR EXTERNAL USE ONLY.

WHEN USING THIS PRODUCT AVOID CONTACT WITH EYES. IF CONTACT OCCURS, RINSE THOUROUGHLY WITH WATER.

STOP USE AND ASK A DOCTOR IF IRRITATION OR REDNESS DEVELOPS AND LASTS.

purpose

ANTISEPTIC

label

label.jpg